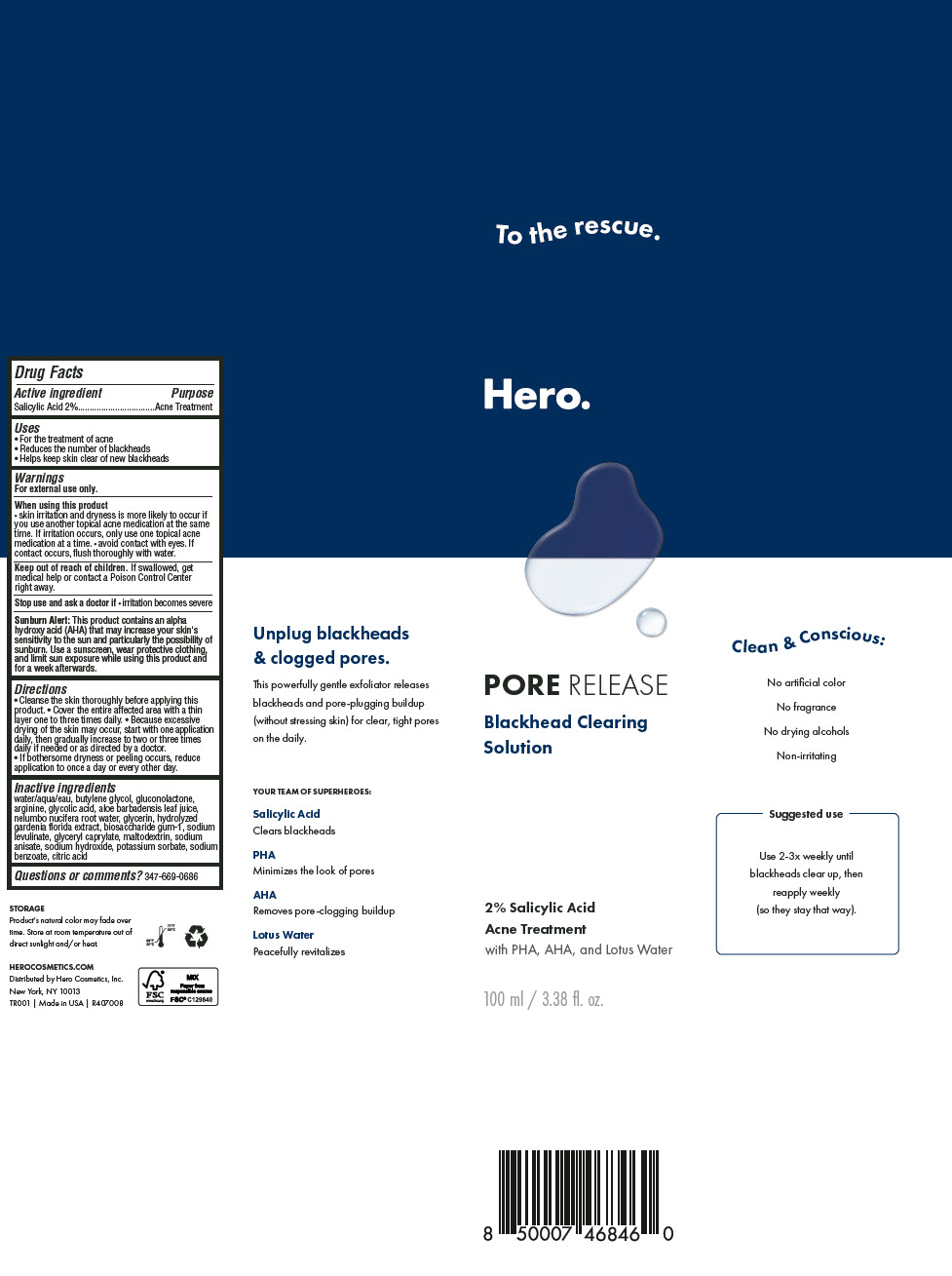 DRUG LABEL: Hero Pore Release Blackhead Clearing
NDC: 10237-001 | Form: LIQUID
Manufacturer: Church & Dwight Co., Inc.
Category: otc | Type: HUMAN OTC DRUG LABEL
Date: 20251205

ACTIVE INGREDIENTS: SALICYLIC ACID 20 mg/1 mL
INACTIVE INGREDIENTS: WATER; BUTYLENE GLYCOL; GLUCONOLACTONE; ARGININE; GLYCOLIC ACID; ALOE VERA LEAF; NELUMBO NUCIFERA ROOT OIL; GLYCERIN; BIOSACCHARIDE GUM-1; SODIUM LEVULINATE; GLYCERYL MONOCAPRYLATE; MALTODEXTRIN; SODIUM ANISATE; SODIUM HYDROXIDE; POTASSIUM SORBATE; SODIUM BENZOATE; CITRIC ACID MONOHYDRATE

Hero Pore Release Blackhead Clearing Solution

Drug Facts

Active ingredient

Salicylic Acid 2%

Purpose

Acne Treatment

Uses

- For the treatment of acne
- Reduces the number of blackheads
- Helps keep skin clear of new blackheads

Warnings

For external use only.

When using this product

- skin irritation and dryness is more likely to occur if you use another topical acne medication at the same time. If irritation occurs, only use one topical acne medication at a time.
- avoid contact with eyes. If contact occurs, flush thoroughly with water.

Keep out of reach of children.

If swallowed, get medical help or contact a Poison Control Center right away.

Stop use and ask a doctor if

- irritation becomes severe

Sunburn Alert

This product contains an alpha hydroxy acid (AHA) that may increase your skin's sensitivity to the sun and particularly the possibility of sunburn. Use a sunscreen, wear protective clothing, and limit sun exposure while using this product and for a week afterwards.

Directions

- Cleanse the skin thoroughly before applying this product.
- Cover the entire affected area with a thin layer one to three times daily.
- Because excessive drying of the skin may occur, start with one application daily, then gradually increase to two or three times daily if needed or as directed by a doctor.
- If bothersome dryness or peeling occurs, reduce application to once a day or every other day.

Inactive ingredients

water/aqua/eau, butylene glycol, gluconolactone, arginine, glycolic acid, aloe barbadensis leaf juice, nelumbo nucifera root water, glycerin, hydrolyzed gardenia florida extract, biosaccharide gum-1, sodium levulinate, glyceryl caprylate, maltodextrin, sodium anisate, sodium hydroxide, potassium sorbate, sodium benzoate, citric acid

Questions or comments?

347-669-0686

Distributed by Hero Cosmetics, Inc.
New York, NY 10013

PRINCIPAL DISPLAY PANEL - 100 ml Bottle Label

Hero.

PORE RELEASE

Blackhead Clearing
Solution

2% Salicylic Acid
Acne Treatment

with PHA, AHA, and Lotus Water

100 ml / 3.38 fl. oz.